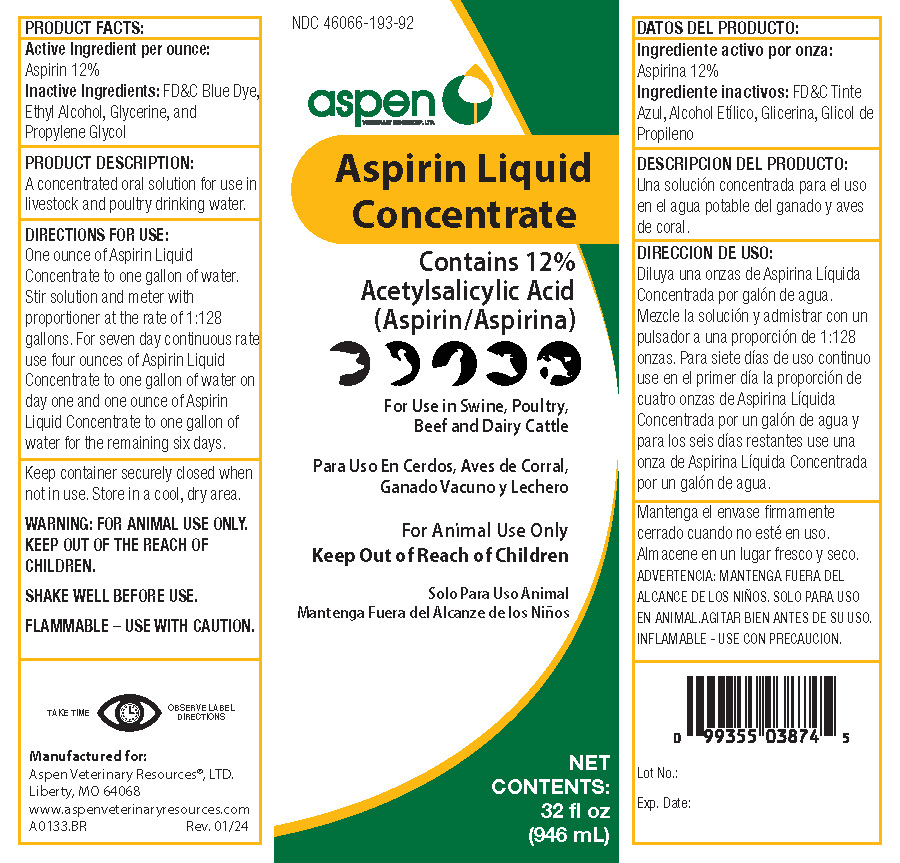 DRUG LABEL: Aspen Aspirin Liquid Concentrate
NDC: 46066-193 | Form: LIQUID
Manufacturer: Aspen Veterinary Resources, Ltd.
Category: animal | Type: OTC ANIMAL DRUG LABEL
Date: 20240205

ACTIVE INGREDIENTS: ASPIRIN 120 g/1 L
INACTIVE INGREDIENTS: FD&C BLUE NO. 1; ALCOHOL; GLYCERIN; PROPYLENE GLYCOL

Aspen Aspirin Liquid Concentrate

PRODUCT FACTS:

- Active ingredient per ounce: Aspirin 12%
- Inactive ingredients: FD&C Blue Dye, Ethyl Alcohol, Glycerine, and Propylene Glycol

PRODUCT DESCRIPTION:

- A concentrated oral solution for use in livestock and poultry drinking water

DIRECTIONS FOR USE:

- One ounce of Aspirin Liquid Concentrate to one gallon of water.
- Stir solution and meter with proportioner at the rate of 1 :128 gallons.
- For seven day continuous rate use four ounces of Aspirin Liquid Concentrate to one gallon of water on day one and one ounce of Aspirin Liquid Concentrate to one gallon of water for the remaining six days.

WARNING:

- FOR ANIMAL USE ONLY.
- KEEP OUT OF REACH OF CHILDREN
- SHAKE WELL BEFORE USE
- FLAMMABLE - USE WITH CAUTION
- Keep container securely closed when not in use. Store in a cool, dry area.
- Take time - Observe Label Directions

PACKAGE LABEL

Add image transcription here...